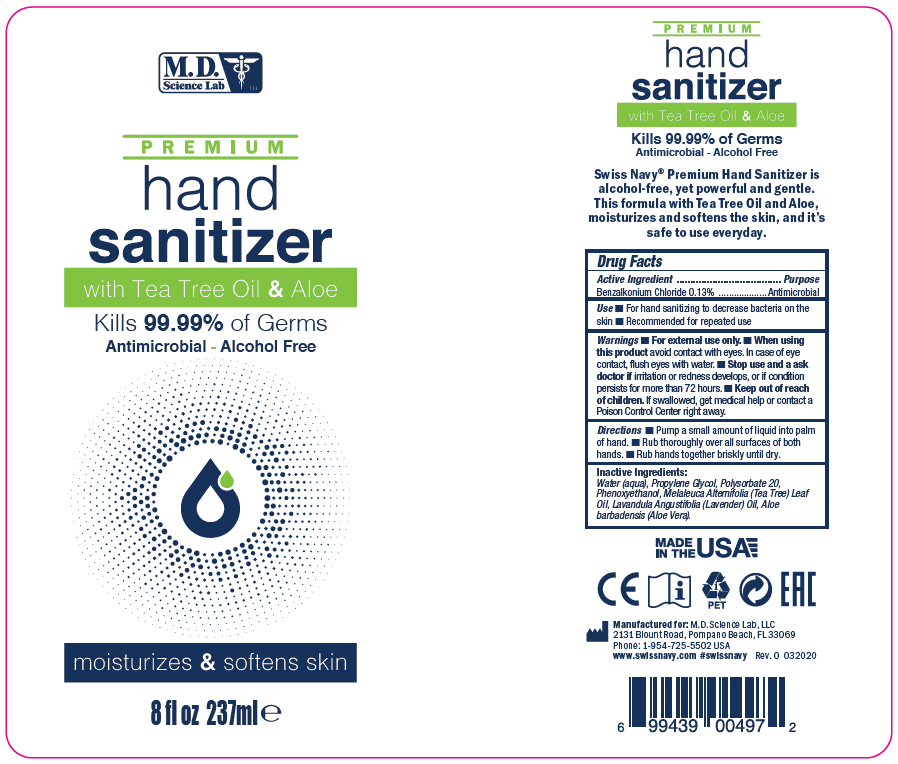 DRUG LABEL: PREMIUM HAND SANITIZER
NDC: 69898-501 | Form: LIQUID
Manufacturer: MD Science Lab LLC
Category: otc | Type: HUMAN OTC DRUG LABEL
Date: 20200429

ACTIVE INGREDIENTS: Benzalkonium Chloride 1.3 mg/1 mL
INACTIVE INGREDIENTS: Water; Propylene Glycol; Phenoxyethanol; LAVENDER OIL; TEA TREE OIL; ALOE VERA LEAF; Polysorbate 20

PREMIUM HAND SANITIZER

Drug Facts

Active Ingredient

Benzalkonium Chloride 0.13%

Purpose

Antimicrobial

Use

- For hand sanitizing to decrease bacteria on the skin
- Recommended for repeated use

Warnings

- For external use only.

- When using this product avoid contact with eyes. In case of eye contact, flush eyes with water.

- Stop use and a ask doctor if irritation or redness develops, or if condition persists for more than 72 hours.

- Keep out of reach of children. If swallowed, get medical help or contact a Poison Control Center right away.

Directions

- Pump a small amount of liquid into palm of hand.
- Rub thoroughly over all surfaces of both hands.
- Rub hands together briskly until dry.

Inactive Ingredients

Water (aqua), Propylene Glycol, Polysorbate 20, Phenoxyethanol, Melaleuca Alternifolia (Tea Tree) Leaf Oil, Lavandula Angustifolia (Lavender) Oil, Aloe barbadensis (Aloe Vera).

PRINCIPAL DISPLAY PANEL - 237 ml Bottle Label

M.D.
Science Lab
LLC

PREMIUM
hand
sanitizer
with Tea Tree Oil & Aloe

Kills 99.99% of Germs

Antimicrobial - Alcohol Free

moisturizes & softens skin

8 fl oz 237ml e